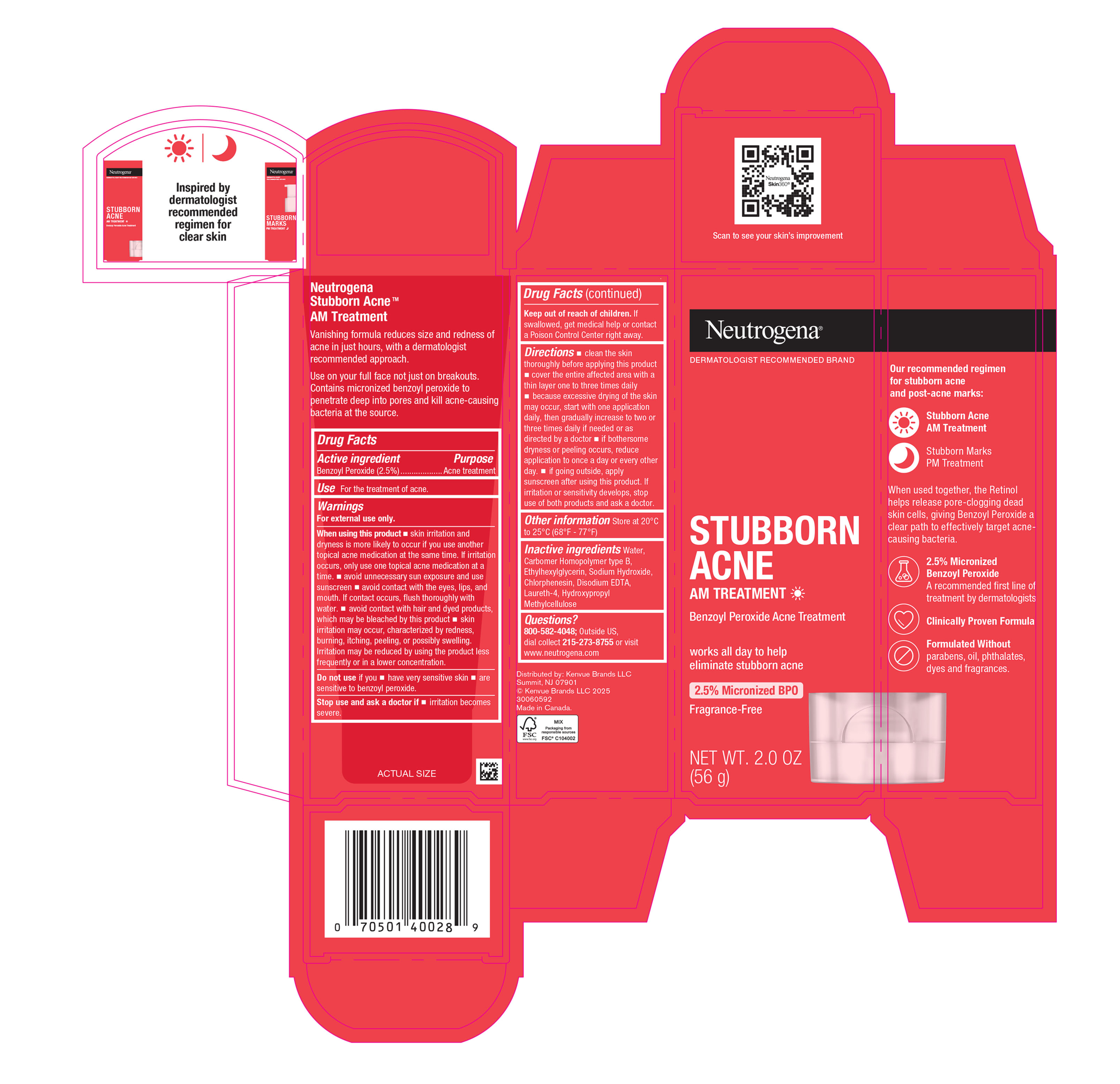 DRUG LABEL: Neutrogena Stubborn Acne AM Treatment
NDC: 69968-0653 | Form: GEL
Manufacturer: Kenvue Brands LLC
Category: otc | Type: HUMAN OTC DRUG LABEL
Date: 20250604

ACTIVE INGREDIENTS: BENZOYL PEROXIDE 25 mg/1 g
INACTIVE INGREDIENTS: WATER; CARBOMER HOMOPOLYMER TYPE B (ALLYL PENTAERYTHRITOL OR ALLYL SUCROSE CROSSLINKED); ETHYLHEXYLGLYCERIN; SODIUM HYDROXIDE; CHLORPHENESIN; EDETATE DISODIUM; LAURETH-4; HYPROMELLOSE, UNSPECIFIED

Neutrogena® STUBBORN ACNE AM TREATMENT

Drug Facts

Active ingredient

Benzoyl Peroxide (2.5%)

Purpose

Acne treatment

Use

For the treatment of acne.

Warnings

For external use only.

When using this product

- skin irritation and dryness is more likely to occur if you use another topical acne medication at the same time. If irritation occurs, only use one topical acne medication at a time.
- avoid unnecessary sun exposure and use a sunscreen
- avoid contact with the eyes, lips and mouth. If contact occurs, flush thoroughly with water
- avoid contact with hair or dyed products, which may be bleached by this product
- skin irritation may occur, characterized by redness, burning, itching, peeling, or possibly swelling. Irritation may be reduced by using the product less frequently or in a lower concentration.

Do not use if you

- have very sensitive skin
- are sensitive to benzoyl peroxide.

Stop use and ask a doctor if

- Irritation becomes severe.

Keep out of reach of children. If swallowed, get medical help or contact a Poison Control Center right away.

Directions

- clean the skin thoroughly before applying this product
- cover the entire affected area with a thin layer one to three times daily
- because excessive drying of the skin may occur, start with one application daily, then gradually increase to two or three times daily if needed or as directed by a doctor
- if bothersome dryness or peeling occurs, reduce application to once a day or every other day.
- If going outside, apply sunscreen after using this product. If irritation or sensitivity develops, stop use of both products and ask a doctor.

Other Information

- Store at 20°C to 25°C (68°F - 77°F)

Inactive ingredients

Water, Carbomer Homopolymer type B, Ethylhexylglycerin, Sodium Hydroxide, Chlorphenesin, Disodium EDTA, Laureth-4, Hydroxypropyl Methylcellulose

Questions?

800-582-4048; Outside US, dial collect 215-273-8755 or visit www.neutrogena.com

Distributed by:
Kenvue Brands LLC
Summit, NJ 07901

PRINCIPAL DISPLAY PANEL - 56 g Tube Carton

Neutrogena®
DERMATOLOGIST RECOMMENDED BRAND
STUBBORN
ACNE
AM TREATMENT
Benzoyl Peroxide Acne treatment

works all day to help
eliminate stubborn acne

2.5% Micronized BPO

Fragrance-Free

NET WT. 2.0 OZ
(56 g)